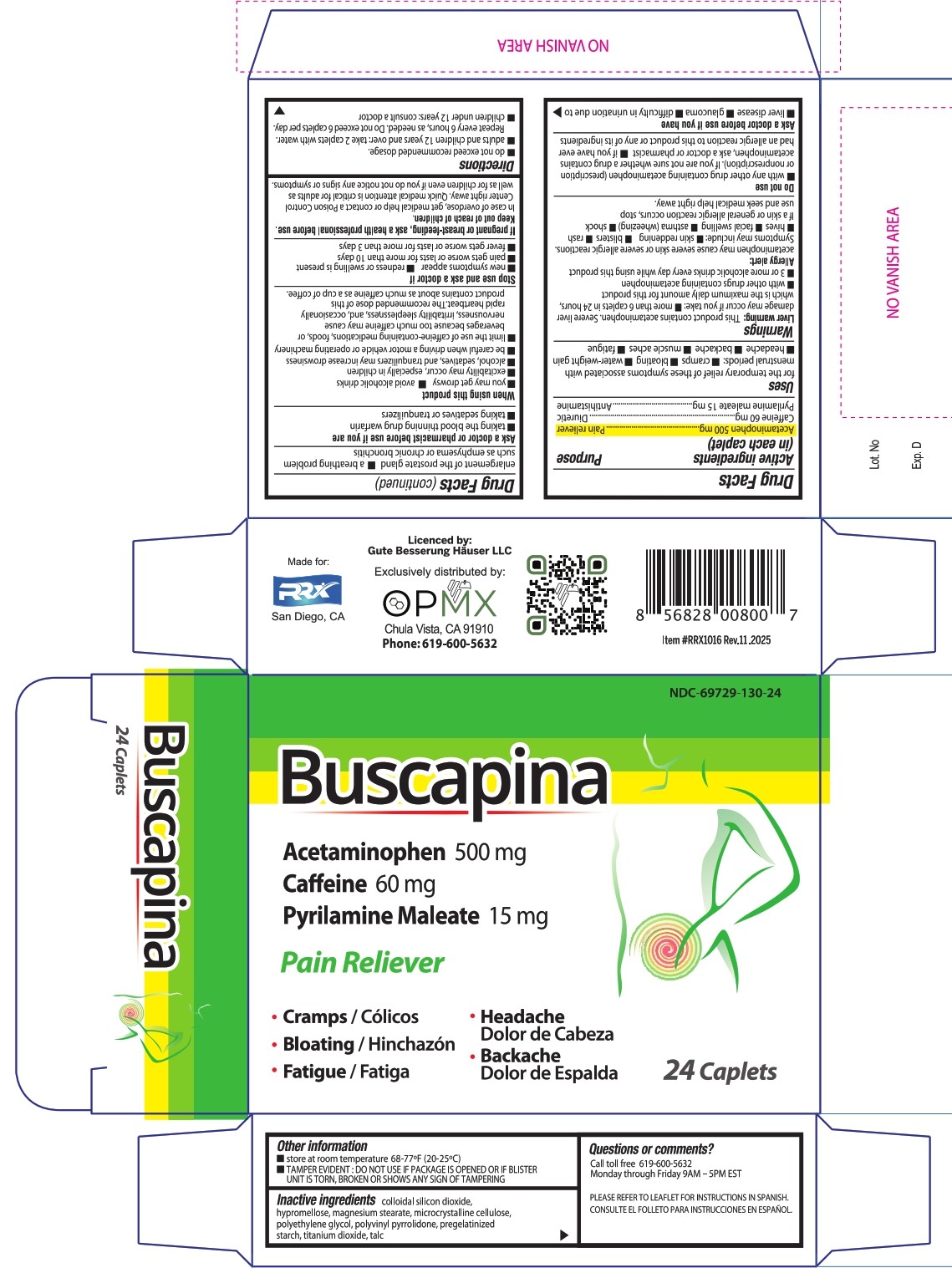 DRUG LABEL: Buscapina
NDC: 69729-130 | Form: TABLET, COATED
Manufacturer: OPMX LLC
Category: otc | Type: HUMAN OTC DRUG LABEL
Date: 20251110

ACTIVE INGREDIENTS: ACETAMINOPHEN 500 mg/1 1; CAFFEINE 60 mg/1 1; PYRILAMINE MALEATE 15 mg/1 1
INACTIVE INGREDIENTS: SILICON DIOXIDE; MAGNESIUM STEARATE; MICROCRYSTALLINE CELLULOSE; STARCH, PREGELATINIZED CORN; TITANIUM DIOXIDE; TALC; HYPROMELLOSES; POLYETHYLENE GLYCOL, UNSPECIFIED; POVIDONE

Buscapina

Drug Facts

Buscapina

Active Ingredients (in each caplet)

Acetaminophen 500mg, Caffeine 60mg, and Pyrilamine maleate 15mg

Purpose

Pain Reliever, Diuretic, Antihistamine, Multi-Symptom Relief

Uses

- For the temporary relief of these symptoms associated with menstrual periods
- Cramps
- Bloating
- Water- weight gain
- Headache
- Backache
- Muscle aches
- Fatigue

Warnings

Liver warning: This product contains acetaminophen. Severe liver damage may occur if you take:

- more than 6 tablets in 24 hours, which is the maximum daily amount for this product
- with other drugs containing acetaminophen
- 3 or more alcoholic drinks every day while using this product.

Allergy warning: Acetaminophen may cause severe skin or severe allergic reactions. Symptoms may include:

- skin reddening
- blisters
- rash
- hives
- facial swelling
- asthma (wheezing)
- shock

If a skin or general allergic reaction occurs, stop use and seek medical help right away.

Do not use

- with any other drug containing acetaminophen (prescription or nonprescription). If you are not sure whether a drug contains acetaminophen, ask a doctor or pharmacist.
- if you have ever had an allergic reaction to this product or any of its ingredients

Ask a doctor before use if you have

- Liver disease
- Glaucoma
- difficulty in urination due to enlargement of the prostate gland
- a breathing problem such as emphysema or chronic bronchitis

Ask a doctor or pharmacist before use if you are

- Taking the blood thinning drug warfarin
- Taking sedatives or tranquilizers

When using this product

- you may get drowsy
- avoid alcoholic drinks
- excitability may occur, especially in children
- alcohol, sedatives, and tranquilizers may increase drowsiness
- be careful when driving a motor vehicle or operating machinery
- limit the use of caffeine-containing medications, foods or beverages because too much caffeine may cause nervousness, irritability, sleeplessness, and occasionally rapid heartbeat. The recommended dose of this product contains aboout as much caffeine as a cup of coffee.

Stop use and ask a doctor if

- new symptoms appear
- redness or swelling is present
- pain gets worse or lasts for more than 10 days
- fever gets worse or lasts for more than 3 days

If pregnant or breast-feeding

Ask a health professional before use.

Keep out of reach of children

In case of overdose, get medical help or contact a Poison Control Center (1-800-222-1222) right away. Quick medical attention is critical for adults as well as for children even if you do not notice any signs or symptoms.

Directions

- Do not exceed recommended dosage.
- Adults and children 12 years and over: Take 2 tablets with water. Repeat every 6 hours, as needed. Do not exceed 6 tablets per day
- Children under 12 years: Consult a doctor

Other Information

- Store at room temperature 68-77° F (20-25°C)
- TAMPER EVIDENT: DO NOT USE IF PACKAGE IS OPENED OR IF BLISTER UNIT IS TORN, BROKEN OR SHOWS ANY SIGN OF TAMPERING

Inactive ingredients

- Colloidal silicon dioxide
- Hypromellose
- Magnesium stearate
- Microcrystalline cellulose
- Polyethylene glycol
- Polyvinyl pyrrolidone
- Pregelatinized starch
- Titanium dioxide
- Talc

Questions or comments?

Call toll free 1-844-832-1138 Monday through Friday 9AM - 5PM EST

PLEASE REFER TO LEAFLET FOR INSTRUCTIONS IN SPANISH

CONSULTE EL FOLLETO PARA INSTRUCCIONES EN ESPAÑOL

Principal display panel 24

NDC 69729-130-24

Buscapina

Acetaminophen 500 mg

Caffeine 60 mg

Pyrilamine Malete 15 mg

Pain Reliever

- Cramps/ Cólicos
- Bloatinng/ Hinchazón
- Fatigue/ Fatiga
- Headache/ Dolor de cabeza
- Backache/ Dolor de espalda

Licenced by:

Gute Besserung Hauser LLC

Exclusively distributed by:

OPMX

Chula Vista, CA 91910

Phone: 619-600-5632